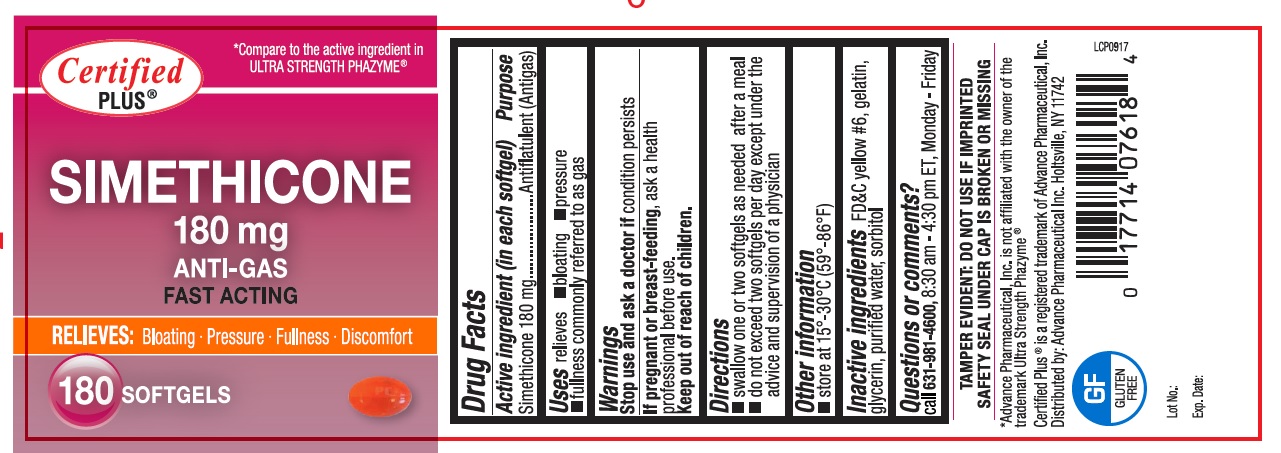 DRUG LABEL: Simethicone
NDC: 17714-076 | Form: GEL
Manufacturer: Advance Pharmaceutical Inc.
Category: otc | Type: HUMAN OTC DRUG LABEL
Date: 20241226

ACTIVE INGREDIENTS: DIMETHICONE 180 mg/1 1
INACTIVE INGREDIENTS: WATER; GELATIN; FD&C YELLOW NO. 6; SORBITOL; GLYCERIN

Certified Plus Anti-Gas SIMETHICONE 180 MG

Active Ingredient

Simethicone 180 mg

Purpose

Antiflatulent

Uses

relieves

- bloating
- pressure
- fullness commonly referred to as gas

Warnings

If pregnant or breast-feeding,ask a health professional before use.

Keep out of reach of children

Directions

- swallow 1 to 2 softgels as needed after meals and at bed time.
- do not exceed 6 tablets per day unless directed by a physician

Other Information

- store at room temperature 15-30 °C (59-86 °F)
- protect from moisture

Inactive Ingredients

FD&C Yellow #6, gelatin, glycerin, purified water, sorbitol

Questions or Comments

TAMPER EVIDENT: DO NOT USE IF IMPRINTED SAFETY SEAL UNDER CAP IS BROKEN OR MISSING

Call 631-981-4600, 8.30 am – 4.30 pm EST Monday - Friday